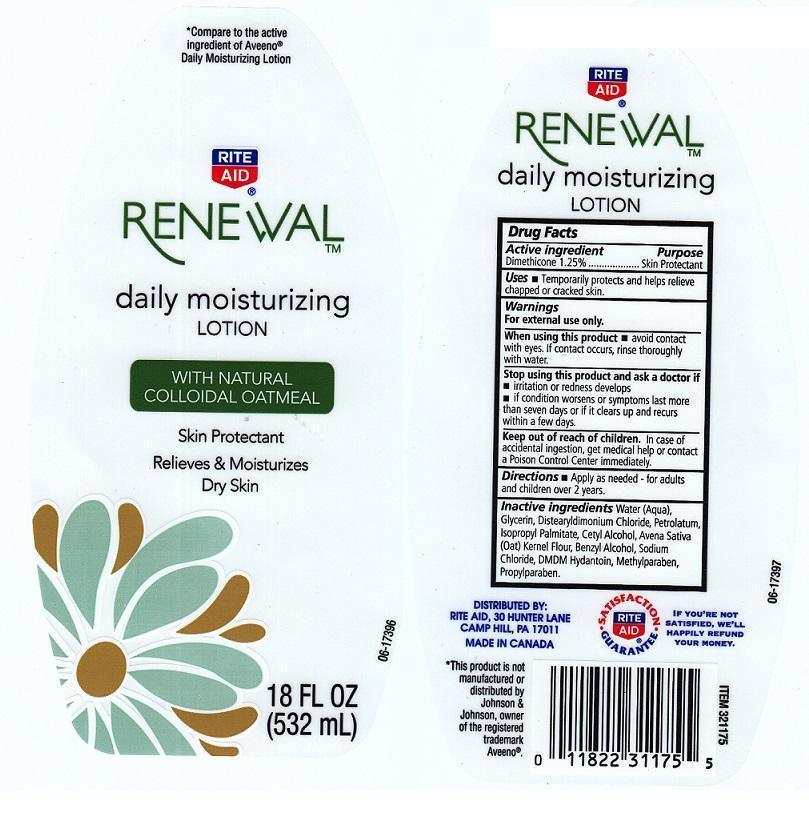 DRUG LABEL: RITE AID RENEWAL
NDC: 11822-3202 | Form: LIQUID
Manufacturer: RITE AID CORPORATION
Category: otc | Type: HUMAN OTC DRUG LABEL
Date: 20120925

ACTIVE INGREDIENTS: DIMETHICONE 12.5 mg/1 mL
INACTIVE INGREDIENTS: WATER; GLYCERIN; DISTEARYLDIMONIUM CHLORIDE; PETROLATUM; ISOPROPYL PALMITATE; CETYL ALCOHOL; OATMEAL; BENZYL ALCOHOL; SODIUM CHLORIDE; DMDM HYDANTOIN; METHYLPARABEN; PROPYLPARABEN

DRUG FACTS

ACTIVE INGREDIENT

DIMETHICONE 1.25%

PURPOSE

SKIN PROTECTANT

USES

TEMPORARILY PROTECTS AND HELPS RELIEVE CHAPPED OR CRACKED SKIN.

WARNINGS

FOR EXTERNAL USE ONLY.

WHEN USING THIS PRODUCT

AVOID CONTACT WITH EYES. IF CONTACT OCCURS, RINSE THOROUGHLY WITH WATER.

STOP USING THIS PRODUCT AND ASK A DOCTOR IF

KEEP OUT OF REACH OF CHILDREN

IN CASE OF ACCIDENTAL INGESTION, GET MEDICAL HELP OR CONTACT A POISON CONTROL CENTER IMMEDIATELY.

DIRECTIONS

APPLY AS NEEDED. FOR ADULTS AND CHILDREN OVER 2 YEARS.

INACTIVE INGREDIENTS

WATER (AQUA), GLYCERIN, DISTEARYLDIMONIUM CHLORIDE, PETROLATUM, ISOPROPYL PALMITATE, CETYL ALCOHOL, AVENA SATIVA (OAT) KERNEL FLOUR, BENZYL ALCOHOL, SODIUM CHLORIDE, DMDM HYDANTOIN, METHYLPARABEN, PROPYLPARABEN.